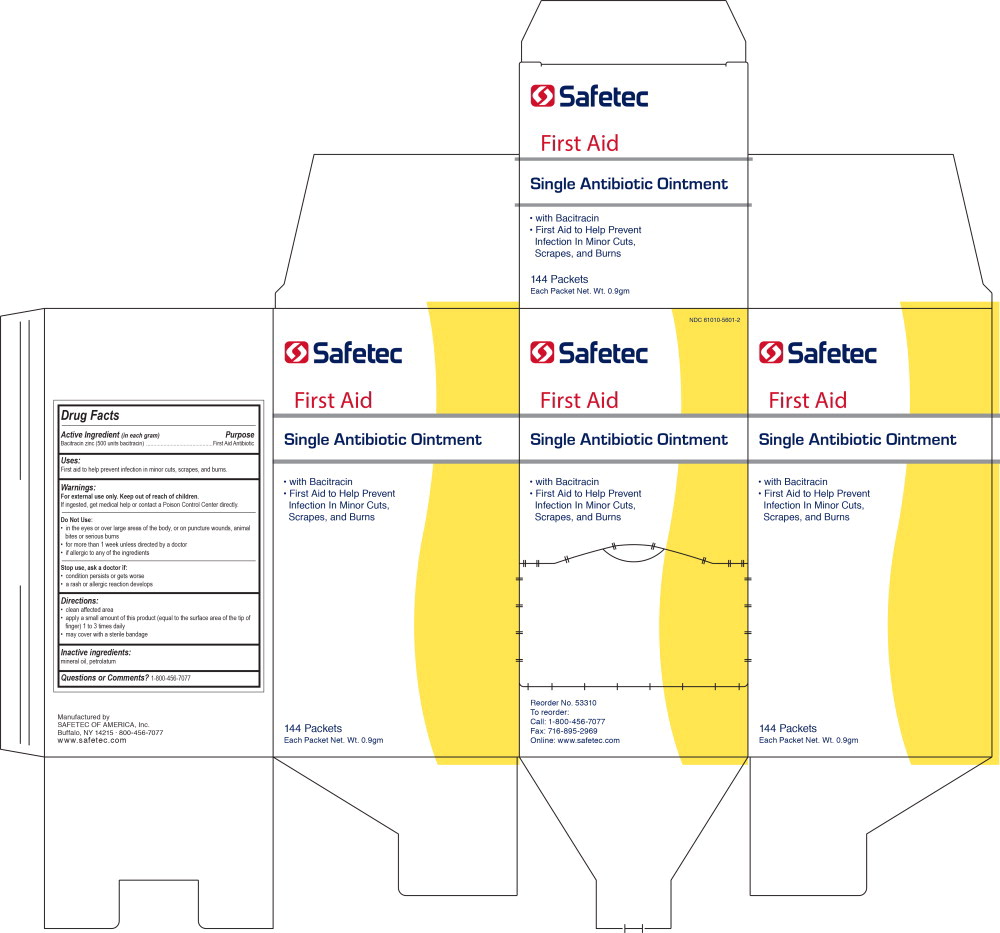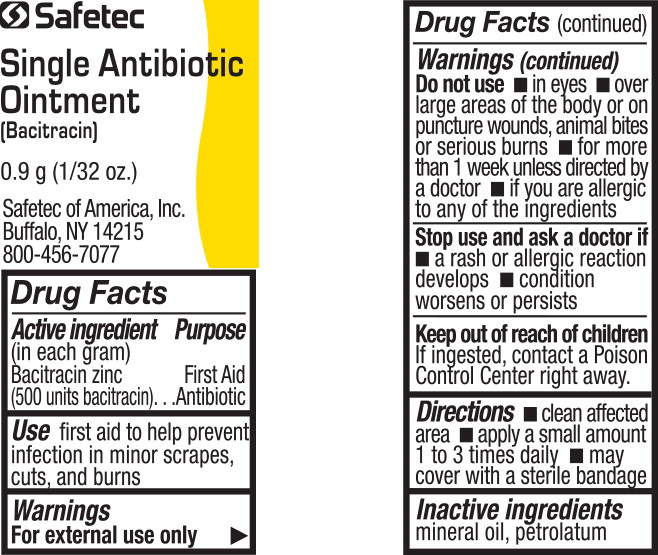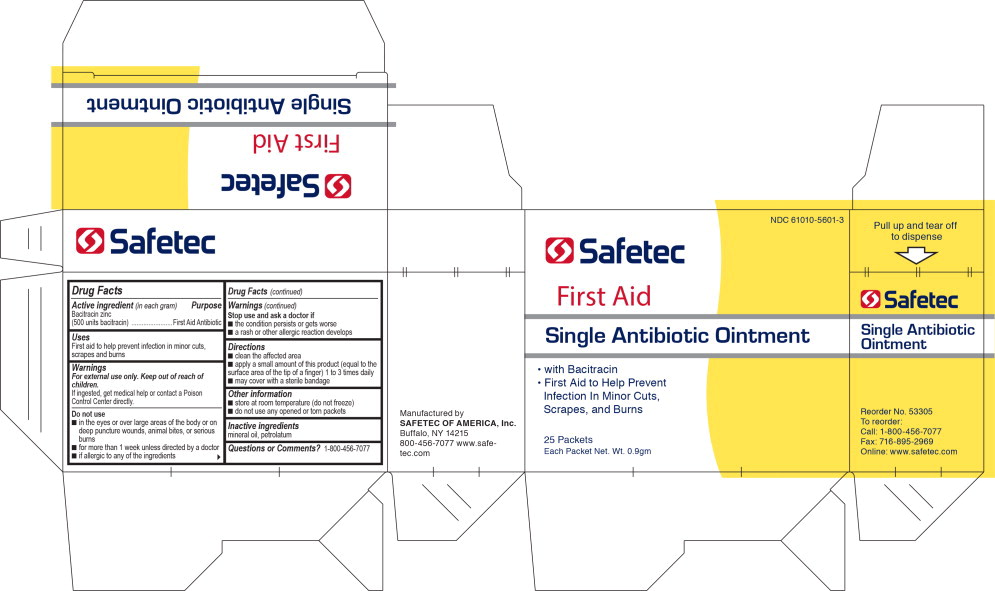 DRUG LABEL: Single Antibiotic with bacitracin
NDC: 61010-5601 | Form: OINTMENT
Manufacturer: Safetec of America
Category: otc | Type: HUMAN OTC DRUG LABEL
Date: 20240214

ACTIVE INGREDIENTS: BACITRACIN ZINC 400 [USP'U]/1 g
INACTIVE INGREDIENTS: PETROLATUM

61010-5601, Single antibiotic with Bacitracin

Drug Facts

Active Ingredient (in each gram)

Bacitracin zinc (500 units bacitracin)

Purpose

First Aid Antibiotic

Uses:

First aid to help prevent infection in minor cuts, scrapes, and burns.

Warnings:

KEEP OUT OF REACH OF CHILDREN

For external use only. Keep out of reach of children.

If ingested, get medical help or contact a Poison Control Center directly.

Do Not Use:

- in the eyes or over large areas of the body, or on puncture wounds, animal bites or serious burns
- for more than 1 week unless directed by a doctor
- if allergic to any of the ingredients

Stop use, ask a doctor if:

- condition persists or gets worse
- a rash or allergic reaction develops

Directions:

- clean affected area
- apply a small amount of this product (equal to the surface area of the tip of finger) 1 to 3 times daily
- may cover with a sterile bandage

Inactive ingredients:

mineral oil, petrolatum

Questions or Comments?

1-800-456-7077

Principal Display Panel - Box Label

NDC 61010-5601-2

Safetec

First Aid

Single Antibiotic Ointment

• with Bacitracin

• First Aid to Help Prevent
Infection In Minor Cuts,
Scrapes, and Burns

Reorder No. 53310

To reorder:

Call: 1-800-456-7077

Fax: 716-895-2969

Online: www.safetec.com

Principal Display Panel - Pouch Label

Safetec

Single Antibiotic
Ointment

(Bacitracin)

0.9 g (1/32 oz.)

Safetec of America, Inc.

Buffalo, NY 14215

800-456-7077

Principal Display Panel - Box Label

NDC 61010-5601-3

Safetec

First Aid

Single Antibiotic Ointment

• with Bacitracin

• First Aid to Help Prevent
Infection In Minor Cuts,
Scrapes, and Burns

25 Packets

Each Packet Net. Wt. 0.9gm